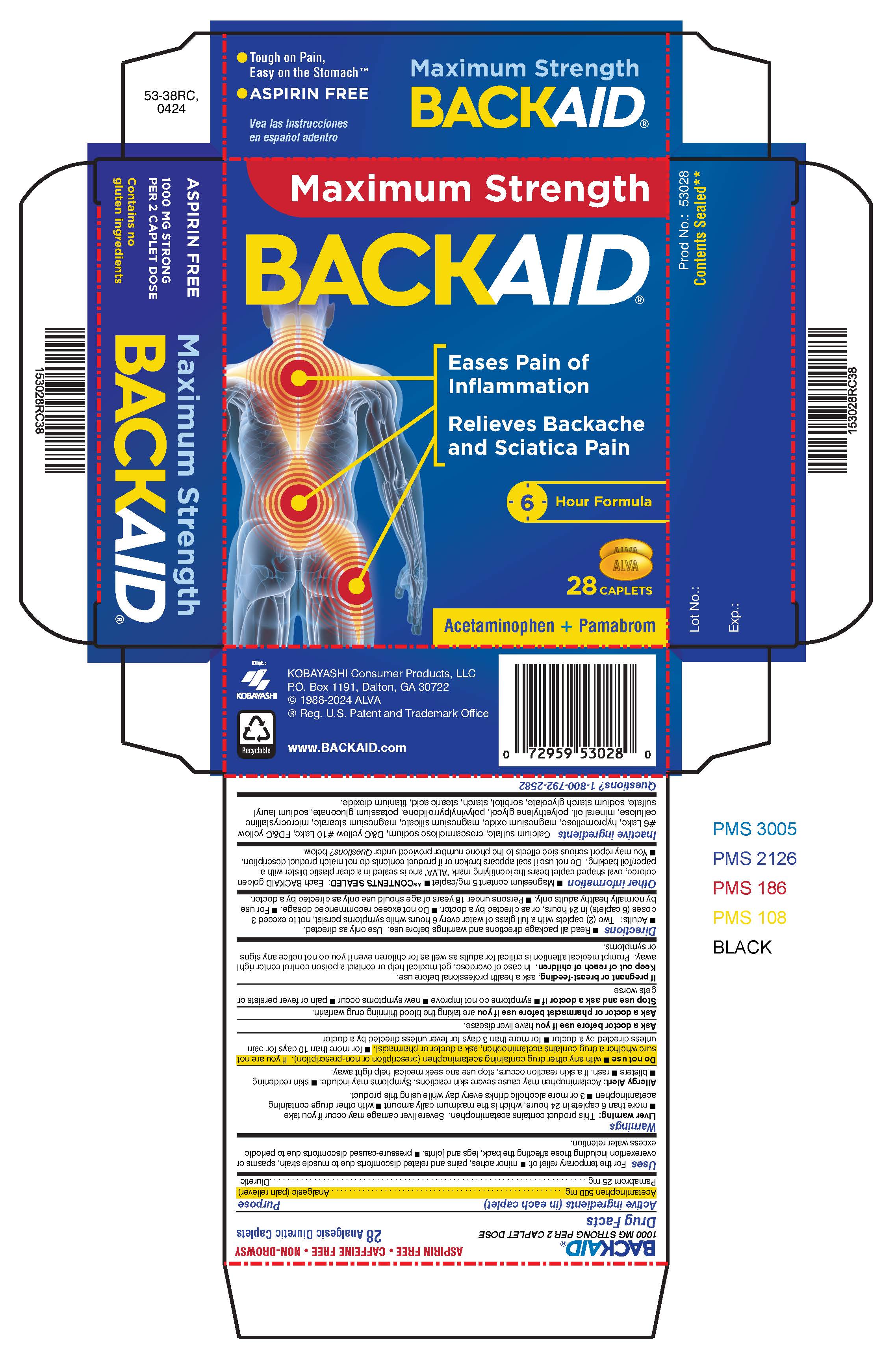 DRUG LABEL: BackAid
NDC: 52389-153 | Form: TABLET, FILM COATED
Manufacturer: Kobayashi Healthcare International, Inc.
Category: otc | Type: HUMAN OTC DRUG LABEL
Date: 20250414

ACTIVE INGREDIENTS: ACETAMINOPHEN 500 mg/1 1; PAMABROM 25 mg/1 1
INACTIVE INGREDIENTS: CALCIUM SULFATE DIHYDRATE; STARCH, CORN; CROSCARMELLOSE SODIUM; D&C YELLOW NO. 10; FD&C YELLOW NO. 6; HYPROMELLOSES; MAGNESIUM OXIDE; TALC; MAGNESIUM STEARATE; CELLULOSE, MICROCRYSTALLINE; LIGHT MINERAL OIL; POLYETHYLENE GLYCOL 400; POTASSIUM GLUCONATE; SODIUM LAURYL SULFATE; SODIUM STARCH GLYCOLATE TYPE A POTATO; SORBITOL; STEARIC ACID; TITANIUM DIOXIDE; POVIDONE

BackAid

Active ingredients (in each caplet)

Acetaminophen, 500 mg

Pamabrom, 25 mg

Purpose

Analgesic (pain reliever)

Diuretic

Uses

For the temporary relief of:

- minor aches, pains and related discomforts due to muscle strain, spasms or overexertion including those affecting the back, legs and joints
- pressure-caused discomforts due to periodic excess water retention

Warnings

Liver Warning: This product contains acetaminophen. Severe liver damage may occur if you take

- more than 6 caplets in 24 hours, which is the maximum daily amount
- with other drugs containing acetaminophen
- 3 or more alcoholic drinks every day while using this product.

Allergy Alert: Acetaminophen may cause severe skin reactions. Symptoms may include:

- skin reddening
- blisters
- rash

If a skin reaction occurs, stop use and seek medical help right away.

Do not use

- with any other drug containing acetaminophen (prescription or non-prescription). If you are not sure whether a drug contains acetaminophen, ask a doctor or pharmacist.
- for more than 10 days for pain unless directed by a doctor
- for more than 3 days for fever unless directed by a doctor

Ask a doctor before use if you have liver disease.

Ask a doctor or pharmacist before use if you are taking the blood thinning drug warfarin.

Stop use and ask a doctor if

- symptoms do not improve
- new symptoms occur
- pain or fever persists or gets worse

PREGNANCY OR BREAST FEEDING

If pregnant or breast-feeding, ask a health professional before use.

Keep out of reach of children. In case of overdose, get medical help or contact a poison control center right away. Prompt medical attention is critical for adults as well as for children even if you do not notice any signs or symptoms.

Directions

- Read all package directions and warnings before use. Use only as directed.
- Adults: Two (2) caplets with a full glass of water every 6 hours while symptoms persist, not to exceed 3 doses (6 caplets) in 24 hours, or as directed by a doctor.
- Do not exceed recommended dosage.
- For use by normally healthy adults only.
- Persons under 18 years of age should use only as directed by a doctor.

Other information

- Magnesium content: 5 mg/caplet
- **CONTENTS SEALED: Each BACKAID MAX golden-colored, oval shaped caplet bears the identifying mark "ALVA" and is sealed in a clear plastic blister with a paper/foil backing. Do not use if seal appears broken or if product contents do not match product description.
- You may report serious side effects to the phone number provided under Questions? below.

INACTIVE INGREDIENT

Inactive ingredients Calcium sulfate, croscarmellose sodium, D&C yellow #10 Lake, FD&C yellow #6 Lake, hypromellose, magnesium oxide, magnesium stearate, microcrystalline cellulose, mineral oil, polyethylene glycol, polyvinylpyrrolidone, potassium gluconate, sodium lauryl sulfate, sodium starch glycolate, sorbitol, starch, stearic acid, talc, titanium dioxide.

Questions? 1-800-792-2582.

Package insert

Aspirin Free

Backache Relief

BACKAID Max

1000 mg Strong per 2 Caplet Dose

Maximum Strength 6 Hour Formula

Active ingredients: Each caplet contains: acetaminophen 500 mg (analgesic/pain reliever) and pamabrom 25 mg (diuretic).

Uses: For the temporary relief of: • minor aches, pains and related discomforts due to muscle strain, spasms or overexertion including those affecting the back, legs and joints. • pressure-caused discomforts due to periodic excess water retention.

Warnings

Liver Warning: This product contains acetaminophen. Severe liver damage may occur if you take • more than 6 caplets in 24 hours, which is the maximum dally amount • with other drugs containing acetaminophen • 3 or more alcoholic drinks every day while using this product.

Allergy Alert: Acetaminophen may cause severe skin reactions. Symptoms may include • skin reddening • blisters • rash. If a skin reaction occurs, stop use and seek medical help right away.

Do not use • with any other drug containing acetaminophen (prescription or non-prescription). If you are not sure whether a drug contains acetaminophen, ask a doctor or pharmacist. • for more than 10 days for pain unless directed by a doctor • for more than 3 days for fever unless directed by a doctor.

Ask a doctor before use if you have liver disease.

Ask a doctor or pharmacist before use if you are taking the blood thinning drug warfarin.

Stop use and ask a doctor if

- symptoms do not improve
- new symptoms occur
- pain or fever persists or gets worse

If pregnant or breast feeding, ask a health professional before use.

Keep out of reach of children. In case of overdose, get medical help or contact a poison control center right away. Prompt medical attention is critical for adults as well as for children even if you do not notice any signs or symptoms.

Directions:

- Read all package directions and warnings before use. Use only as directed.
- Adults: Two (2) caplets with a full glass of water every 6 hours while symptoms persist, not to exceed 3 doses (6 caplets) in 24 hours, or as directed by a doctor.
- Do not exceed recommended dosage.
- For use by normally healthy adults only.
- Persons under 18 years of age should use only as directed by a doctor.

Other information:

Magnesium content: 5 mg/caplet

**CONTENTS SEALED: Each BACKAID MAX golden-colored, oval shaped caplet bears the identifying mark "ALVA" and is sealed in a clear plastic blister with a paper/foil backing. Do not use if seal appears broken or if product contents do not match product description. • You may report serious side effects to the phone number provided under Questions? below.

Inactive ingredients Calcium sulfate, croscarmellose sodium, D&C yellow #10 Lake, FD&C yellow #6 Lake, hypromellose, magnesium oxide, magnesium stearate, microcrystalline cellulose, mineral oil, polyethylene glycol, polyvinylpyrrolidone, potassium gluconate, sodium lauryl sulfate, sodium starch glycolate, sorbitol, starch, stearic acid, talc and titanium dioxide.

Questions? 1-800-792-2582